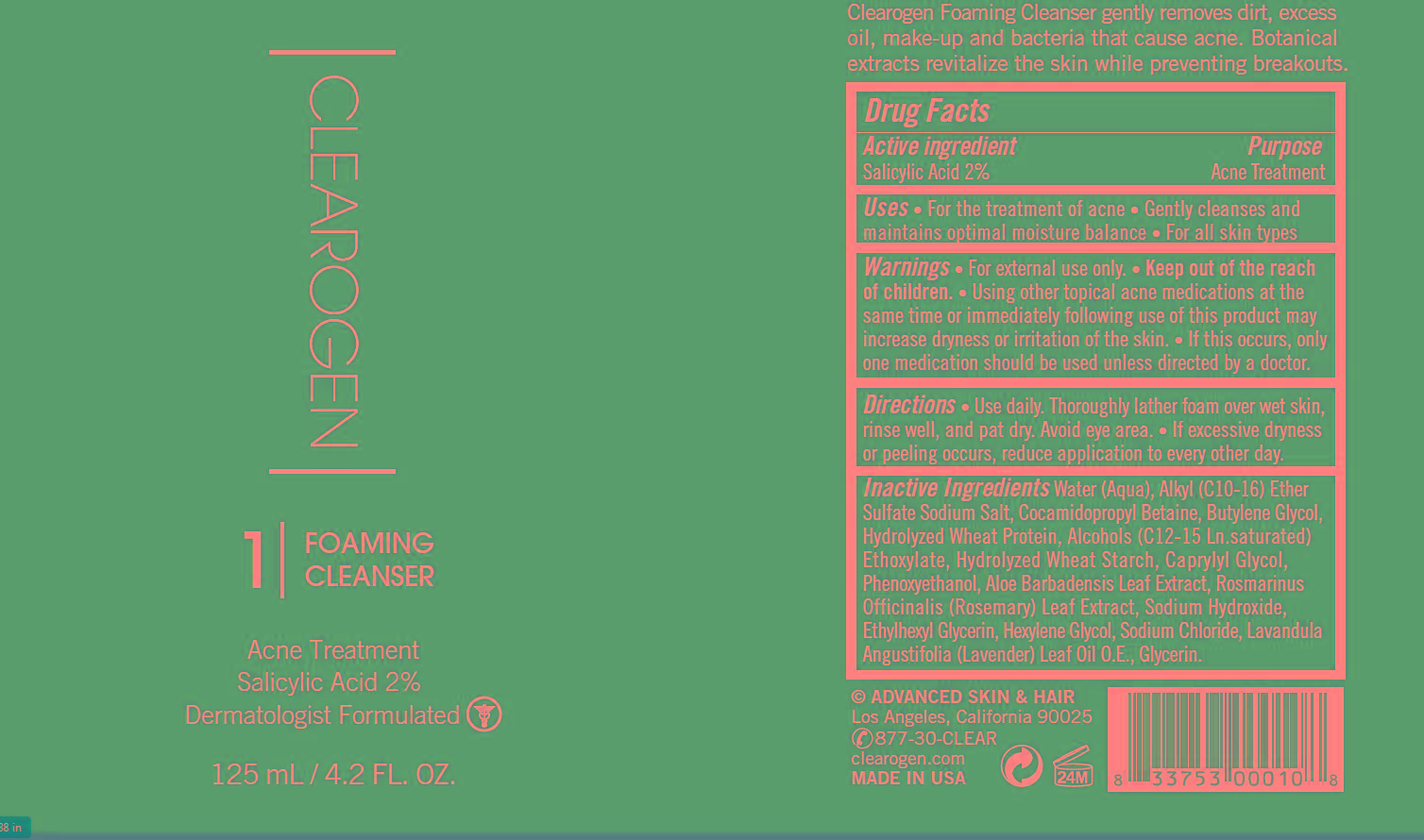 DRUG LABEL: Foaming Cleanser
NDC: 62742-4168 | Form: LIQUID
Manufacturer: Allure Labs Inc
Category: otc | Type: HUMAN OTC DRUG LABEL
Date: 20181109

ACTIVE INGREDIENTS: SALICYLIC ACID 20 mg/1 mL
INACTIVE INGREDIENTS: WATER; COCAMIDOPROPYL BETAINE; BUTYLENE GLYCOL; HYDROLYZED WHEAT PROTEIN (ENZYMATIC, 3000 MW); C12-15 ALCOHOLS; CAPRYLYL GLYCOL; PHENOXYETHANOL ; ALOE VERA LEAF; ROSEMARY; SODIUM HYDROXIDE; ETHYLHEXYLGLYCERIN; HEXYLENE GLYCOL; SODIUM CHLORIDE; LAVENDER OIL; GLYCERIN

DRUG FACTS

Active Ingredient: Salicylic Acid 2%

Purpose: Acne Treatment

Uses:

- For the treatment of acne
- Gently cleanses and maintains optimal moisture balance
- For all skin types

Warnings: For external use only.

Keep out of the reach of children

WHEN USING

- Using other topical acne medications at the same time or immediately following use of this product may increase dryness or irritation of the skin.
- If this occurs, only one medication should be used unless directed by a doctor.

Directions:

- Use daily.
- Thoroughly lather foam over wet skin, rinse well and pat dry.
- Avoid eye area.
- If excessive dryness or peeling occurs, reduce application to every other day.

INACTIVE INGREDIENT

Water (Aqua), Alkyl (C10-16) Ether Sulfate Sodium Salt, Cocamidopropyl Betaine, Butylene Glycol, Hydrolyzed Wheat Protein, Alcohols (C12-15 Ln. saturated) Ethoxylate, Hydrolyzed Wheat Starch, Caprylyl Glycol, Phenoxyethanol, Aloe Barbadensis Leaf Extract, Rosmarinus Officinalis (Rosemary) Leaf Extract, Sodium Hydroxide, Ethylhexyl Glycerin, Hexylene Glycol Sodium Chloride, Lavandula Angustifolia (Lavender) Leaf Oil O.E., Glycerin.

PACKAGE LABEL

Advanced Skin & Hair

Los Angeles, California 90025

877-30-CLEAR

clearogen.com

Made In USA